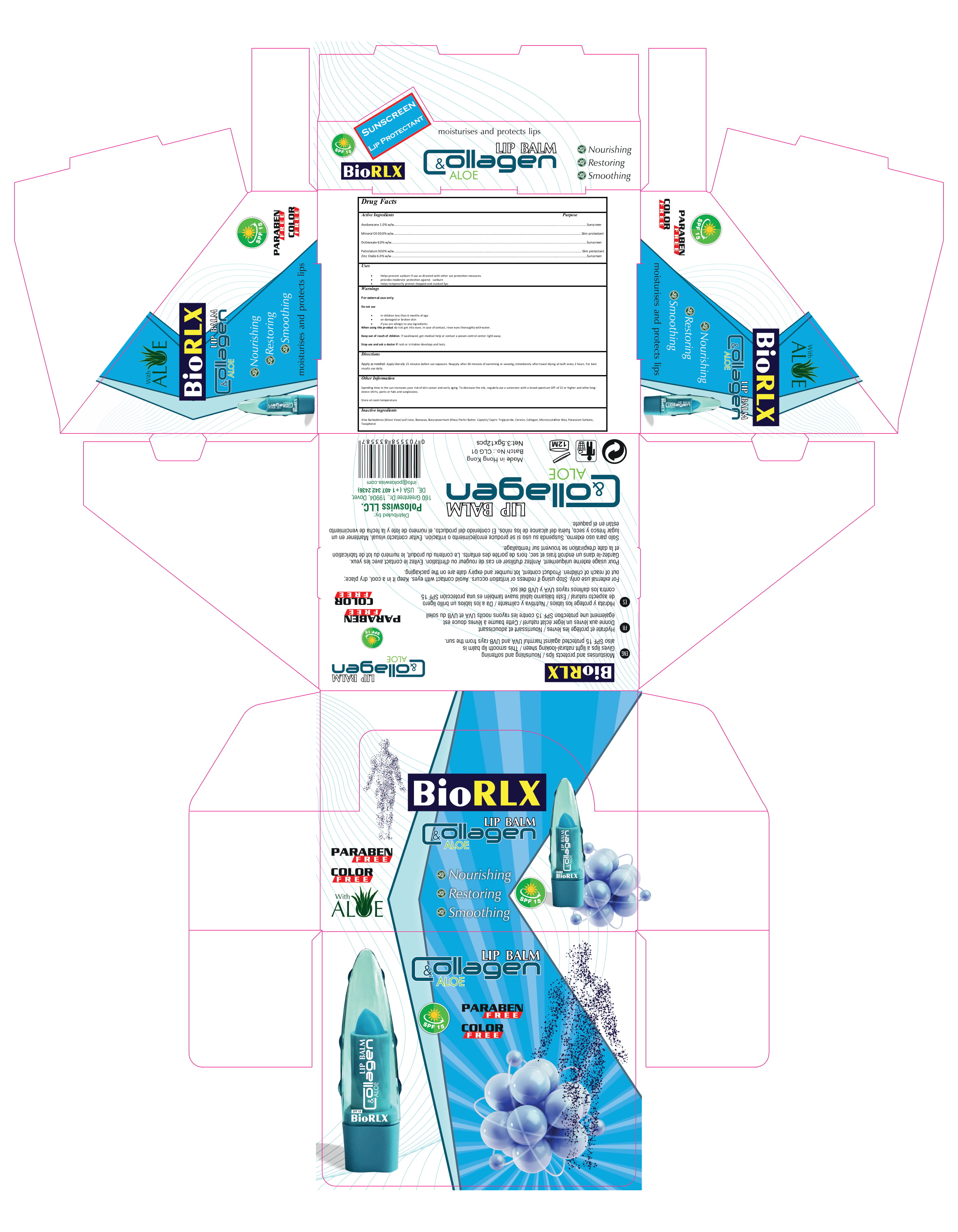 DRUG LABEL: BIORLX LIP BALM COLLAGEN
NDC: 80554-002 | Form: STICK
Manufacturer: LOTUSA LLC.
Category: otc | Type: HUMAN OTC DRUG LABEL
Date: 20200918

ACTIVE INGREDIENTS: AVOBENZONE 1 g/100 g; ZINC OXIDE 6 g/100 g; OCTINOXATE 6 g/100 g; PETROLATUM 30 g/100 g; MINERAL OIL 30 g/100 g
INACTIVE INGREDIENTS: WHITE WAX; ALOE VERA LEAF; TOCOPHEROL; BUTYROSPERMUM PARKII (SHEA) BUTTER UNSAPONIFIABLES; COLLAGEN ALPHA-1(I) CHAIN BOVINE; MICROCRYSTALLINE WAX; MEDIUM-CHAIN TRIGLYCERIDES; POTASSIUM SORBATE; CERESIN

This is a hand sanitizer manufactured according to the Temporary Policy for Preparation of Certain Alcohol-Based Hand Sanitizer Products During the Public Health Emergency (CoViD-19); Guidance for Industry.

The hand sanitizer is manufactured using only the following United States Pharmacopoeia (USP) grade ingredients in the preparation of the product (percentage in final product formulation) consistent with World Health Organization (WHO) recommendations:

a. Avobenzone 1.0%w/w

b. Mineral Oil 30.0%w/w

c. Octinoxate 6.0% w/w

d. Petrolatum 30.0% w/w

e. Zinc Oxide 6.0% w/w

f. Aloe Barbadensis (Alove Vera) Leaf Juice

g. Beeswax

h. Butyrpsoermum (Shea) Parkii Butter

i.Caprylic/ Capric Triglyceride

j. Ceresin

k.Collagen

l. Microcrystalline Wax

m. Potassium Sorbate

n. Tocopherol

The firm does not add other active or inactive ingredients. Different or additional ingredients may impact the quality and potency of the product.

Active Ingredient(s)

Avobenzone 1.0% w/w Sunscreen
Mineral Oil 30.0% w/w Skin protectant
Octinoxate 6.0% w/w Sunscreen
Petrolatum 30.0% w/w Skin protectant
Zinc Oxide 6.0% w/w Sunscreen

Purpose

Sunscreen, Skin protectant, Lip Balm

Use

Helps prevent sunburn if use as directed with other sun protection measures.
provides moderate protection against sunburn
Helps temporarily protect chapped and cracked lips.

Warnings

For external use only.

Do not use

in children less than 6 months of age on damaged or broken skin if you are allergic to any ingredients

When using this product keep out of eyes, ears, and mouth. In case of contact with eyes, rinse eyes thoroughly with water.
Stop use and ask a doctor if irritation or rash occurs. These may be signs of a serious condition.
Keep out of reach of children. If swallowed, get medical help or contact a Poison Control Center right away.

Stop use and ask a doctor if rash or irritation develops and lasts.

Keep out of reach of children. If swallowed, get medical help or contact a Poison Control Center right away.

Directions

Apply as needed. Apply liberally 15 minutes before sun exposure. Reapply after 60 minutes of swimming or sweatig, immediately after towel drying at leaft every 2 hours. For best results use daily.

Other information

- Spending time in the sun increases your risk of skin cancer and early aging. To decrease the risk, regularly use a sunscreen with a broad spectrum SPF of 15 or higher and other longsleeve shirts, pants or hats and sunglassess.
  Store at room temperature

Inactive ingredients

Aloe Barbadensis (Alove Vera) Leaf Juice, Beeswax, Butyrpsoermum (Shea) Parkii Butter, Caprylic/ Capric Triglyceride, Ceresin, Collagen, Microcrystalline Wax, Potassium Sorbate, Tocopherol

Package Label - Principal Display Panel

12x3.5 g NDC:80554-002-01